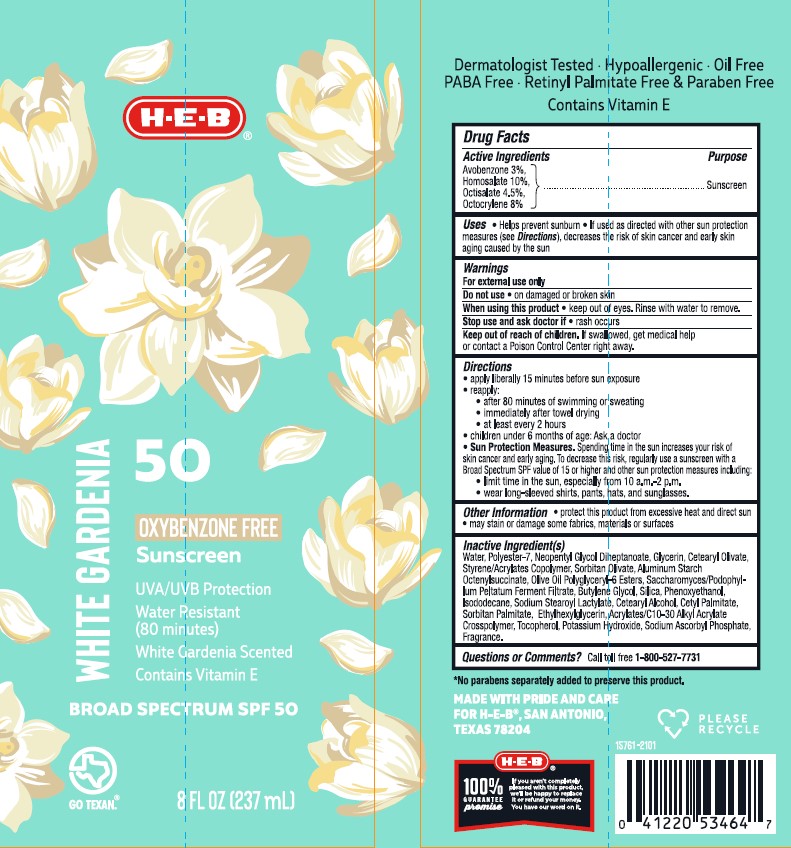 DRUG LABEL: HEB SPF 50 White Gardenia Sunscreen
NDC: 37808-073 | Form: LOTION
Manufacturer: H.E.B
Category: otc | Type: HUMAN OTC DRUG LABEL
Date: 20241015

ACTIVE INGREDIENTS: AVOBENZONE 30 mg/1 mL; HOMOSALATE 100 mg/1 mL; OCTISALATE 45 mg/1 mL; OCTOCRYLENE 80 mg/1 mL
INACTIVE INGREDIENTS: WATER; SILICON DIOXIDE; SODIUM ASCORBYL PHOSPHATE; ALUMINUM STARCH OCTENYLSUCCINATE; ETHYLHEXYLGLYCERIN; .ALPHA.-TOCOPHEROL, DL-; POLYESTER-7; NEOPENTYL GLYCOL DIHEPTANOATE; ISODODECANE; BUTYLENE GLYCOL; POTASSIUM HYDROXIDE; GLYCERIN; PHENOXYETHANOL; CARBOMER COPOLYMER TYPE A; CETYL PALMITATE; CETOSTEARYL ALCOHOL; PODOPHYLLUM; SORBITAN OLIVATE; OLIVE OIL POLYGLYCERYL-6 ESTERS; CETEARYL OLIVATE; SORBITAN MONOPALMITATE; BUTYL METHACRYLATE/METHYL METHACRYLATE/METHACRYLIC ACID/STYRENE CROSSPOLYMER

HEB SPF 50 White Gardenia Sunscreen Lotion

Active Ingredients

Avobenzone 3.0%, Homosalate 10.0%, Octisalate 4.5%, Octocrylene 8.0%

Purpose

Sunscreen

Uses

- helps prevent sunburn
- if used as directed with other sun protetion measures (see Directions), decreases the risk of skin cancer and early skin aging caused by the sun

Warnings

For external use only

Do not use

• on damaged or broken skin.

When using this product

• keep out of eyes. Rinse with water to remove.

Stop use and ask a doctor if

• rash occurs.

Keep out of reach of children.

If swallowed, get medical help or contact a Poison Control Center right away.

Directions

- apply liberally 15 minutes before sun exposure
- reapply:

• after 80 minutes of swimming or sweating

• immediately after towel drying

• at least every 2 hours

- children under 6 months of age: Ask a doctor
- Sun Protection Measures. Spending time in the sun increases your risk of skin cancer and early skin aging. To decrease this risk, regularly use a sunscreen with a Broad Spectrum SPF value of 15 or higher and other sun protection measures including:

• limit time in the sun, especially from 10 a.m. - 2 p.m.

• wear long-sleeved shirts, pants, hats, and sunglasses

Other Information

- protect the product in this container from excessive heat and direct sun
- may stain or damage some fabrics, materials or surfaces

Inactive Ingredient(s)

water, polyester-7, neopentyl glycol diheptanoate, glycerin, cetearyl olivate, styrene/acrylates copolymer, sorbitan olivate, aluminum starch octenylsuccinate, olive oil polyglyceryl-6 esters, saccharomyces/podophyllum peltatum ferment filtrate, butylene glycol, silica, phenoxyethanol, isododecane, sodium stearoyl lactylate, cetearyl alcohol, cetyl palmitate, sorbitan palmitate, ethylhexylglycerin, acrylates/C10-30 alkyl acrylate crosspolymer, tocopherol (vitamin E), potassium hydroxide, sodium ascorbyl phosphate, fragrance.